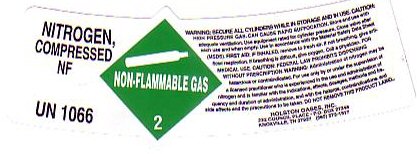 DRUG LABEL: NITROGEN
NDC: 55050-0006 | Form: GAS
Manufacturer: Holston Gases, Inc
Category: prescription | Type: HUMAN PRESCRIPTION DRUG LABEL
Date: 20100101

ACTIVE INGREDIENTS: NITROGEN 99 L/100 L

NITROGEN NF COMPRESSED LABEL

NITROGEN COMPRESSED NF - UN 1066 - NON-FLAMMABLE GAS - 2 - FOR MEDICAL USE. CAUTION: FEDERAL LAW PROHIBITS DISPENSING WITHOUT A PRESCRIPTION. WARNING: ADMINISTRATION OF NITROGEN MAY BE HAZARDOUS OR CONTRAINDICATED. FOR USE ONLY BY OR UNDER THE SUPERVISION OF A LICENSED PRACTITIONER WHO IS EXPERIENCED IN THE USE AND ADMINISTRATION OF NITROGEN AND IS FAMILIAR WITH THE INDICATIONS, EFFECTS, DOSAGES, METHODS AND FREQUENCY AND DURATION OF ADMINISTRATION, AND WITH THE HAZARDS CONTRAINDICATIONS AND SIDE EFFECTS AND THE PRECAUTIONS TO BE TAKEN.

GENERAL WARNINGS AND PRECAUTIONS

WARNING: SECURE ALL CYLINDERS WHILE IN STORAGE AND IN USE. CAUTION: HIGH PRESSURE GAS CAN CAUSE RAPID SUFFOCATION. STORE AND USE WITH ADEQUATE VENTILATION. USE EQUIPMENT RATED FOR CYLINDER PRESSURE. CLOSE VALVE AFTER EACH USE AND WHEN EMPTY. USE IN ACCORDANCE WITH MATERIAL SAFETY DATA SHEET (MSDS). FIRST AID: IF INHALED REMOVE TO FRESH AIR. IF NOT BREATHING GIVE ARTIFICIAL RESPIRATION. IF BREATHING DIFFICULT GIVE OXYGEN. CALL A PHYSICIAN. DO NOT REMOVE THIS PRODUCT LABEL